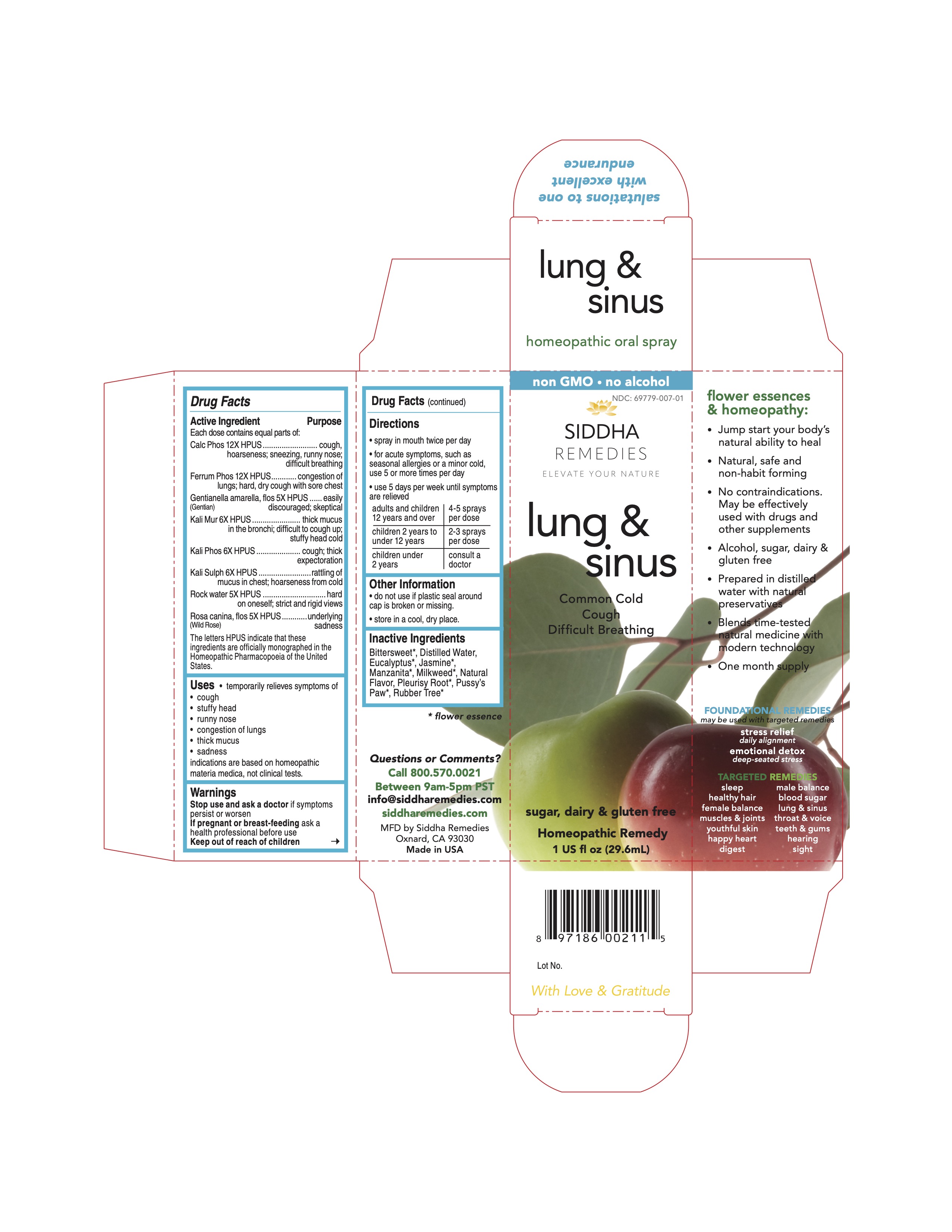 DRUG LABEL: lung and sinus
NDC: 69779-007 | Form: SPRAY
Manufacturer: Siddha Flower Essences LLC
Category: homeopathic | Type: HUMAN OTC DRUG LABEL
Date: 20251231

ACTIVE INGREDIENTS: TRIBASIC CALCIUM PHOSPHATE 12 [hp_X]/29.6 mL; FERROSOFERRIC PHOSPHATE 12 [hp_X]/29.6 mL; GENTIANELLA AMARELLA FLOWER 5 [hp_X]/29.6 mL; POTASSIUM CHLORIDE 6 [hp_X]/29.6 mL; POTASSIUM PHOSPHATE, DIBASIC 6 [hp_X]/29.6 mL; POTASSIUM SULFATE 6 [hp_X]/29.6 mL; WATER 5 [hp_X]/29.6 mL; ROSA CANINA FLOWER 5 [hp_X]/29.6 mL
INACTIVE INGREDIENTS: SOLANUM DULCAMARA FLOWER; ASCLEPIAS TUBEROSA FLOWERING TOP

Drug Facts

Active Ingredient

Each dose contains equal parts of:

Calc Phos 12X HPUS
Ferrum Phos 12X HPUS
Gentianella amarella, flos (Gentian) 5X HPUS
Kali Mur 6X HPUS
Kali Phos 6X HPUS
Kali Sulph 6X HPUS
Rock water 5X HPUS
Rosa Canina, flos (Wild Rose) 5X HPUS

Purpose

Each dose contains equal parts of:
Calc Phos 12X HPUS...............................................cough; hoarseness; sneezing; runny nose; difficult breathing
Ferrum Phos 12X HPUS...........................................congestion of lungs; hard, dry cough with sore chest
Gentianella amarella, flos (Gentian) 5X HPUS............easily discouraged; skeptical
Kali Mur 6X HPUS...................................................thick mucus in the bronchi; difficult to cough up; stuffy head cold
Kali Phos 6X HPUS.................................................cough; thick expectoration
Kali Sulph 6X HPUS.................................................rattling of mucus in chest; hoarseness from cold
Rock water 5X HPUS...............................................hard on oneself; strict and rigid views
Rosa Canina, flos (Wild Rose) 5X HPUS....................underlying sadness
The letters HPUS indicate that these ingredients are officially monographed in the Homeopathic Pharmacopoeia of the United States.

Uses

- temporarily relieves symptoms of
- cough
- stuffy head
- runny nose
- congestion of lungs
- thick mucus
- sadness

indications are based on homeopathic materia medica, not clinical tests.

Warnings

Stop use and ask a doctor if symptoms persist or worsen

PREGNANCY OR BREAST FEEDING

If pregnant or breast-feeding ask a health professional before use

Keep out of reach of children

Directions

- spray in mouth twice per day
- for acute symptoms, such as seasonal allergies or a minor cold, use 5 or more times per day
- use 5 days per week until symptoms are relieved

adults and children 12 years and over | 4-5 sprays per dose
children 2 years to under 12 years | 2-3 sprays per dose
children under 2 years | consult a doctor

Other Information

- do not use if plastic seal around cap is broken or missing.
- store in a cool, dry place.

Inactive Ingredients

Bittersweet*, Eucalyptus*, Jasmine*, Manzanita*, Milkweed*, Natural Flavor, Pleurisy Root*, Purified Water, Pussy's Paw*, Rubber Tree*

*flower essence

Questions or Comments?

Call 800.570.0021
Between 9am-5pm PST
info@siddhaflowers.com
siddhaflowers.com

MFD by Siddha Flower Essences
Oxnard, CA 93030

Made in USA

Side Panel

flower essences and homeopathy:

- Jump start your body's natural ability to heal
- Natural, safe and non-habit forming
- No contraindications. May be effectively used with drugs and other supplements
- Alcohol, sugar, dairy and gluten free
- Prepared in purified water with natural preservatives
- Blends time-tested natural medicine with modern technology
- One month supply

FOUNDATIONAL REMEDIES
may be used with targeted remedies

stress relief
daily alignment
emotional detox
deep-seated stress

TARGETED REMEDIES

sleep male balance
healthy hair blood sugar
female balance lung and sinus
muscles and joints throat and voice
youthful skin teeth and gums
happy heart hearing
digest sight

Principal Display Panel

non GMO - no alcohol
siddha cell salts + flower essences
lung and sinus
Common Cold
Cough
Difficult Breathing
sugar, dairy and gluten free
Homeopathic Remedy
1 US fl oz (29.6mL)